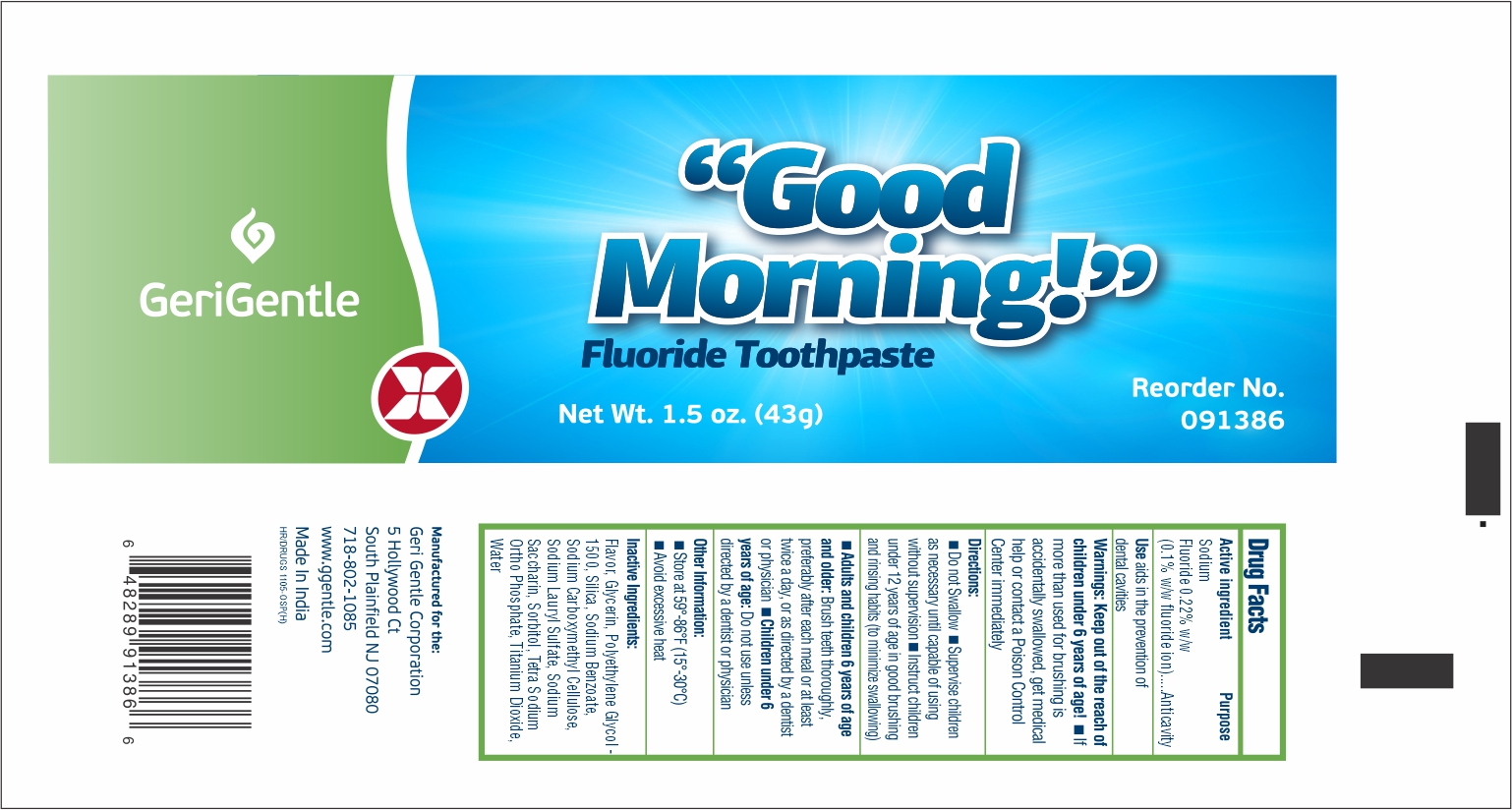 DRUG LABEL: Gerigentle-Good morning
NDC: 69771-091 | Form: PASTE, DENTIFRICE
Manufacturer: Geri-Gentle Corporation
Category: otc | Type: HUMAN OTC DRUG LABEL
Date: 20251023

ACTIVE INGREDIENTS: SODIUM FLUORIDE 0.22 g/100 g
INACTIVE INGREDIENTS: GLYCERIN; POLYETHYLENE GLYCOL 1500; TITANIUM DIOXIDE; WATER; SORBITOL; SILICON DIOXIDE; SODIUM LAURYL SULFATE; CARBOXYMETHYLCELLULOSE SODIUM, UNSPECIFIED FORM; SACCHARIN SODIUM; SODIUM BENZOATE; SODIUM PYROPHOSPHATE

Gerigentle-Good morning New

Drug Facts

Active ingredient

Sodium Fluoride 0.22% w/w

Purpose

Anticavity Toothpaste

Use

aids in the prevention of dental cavities

Warnings

KEEP OUT OF REACH OF CHILDREN

Keep out of the reach of children under 6 years of age!

- If more than used for brushing is accidentally swallowed, get medical help or contact a Poison Control Center immediately

Directions

- Do not Swallow
- Supervise children as necessary until capable of using without supervision
- Instruct children under 12 years of age in good brushing and rinsing habits (to minimize swallowing)
- Adults and children 6 years of age and older:Brush teeth thoroughly, preferably after each meal or at least twice a day, or as directed by a dentist or physician
- Children under 6 years of age:Do not use unless directed by a dentist or physician

Other Information

- Store at 59°-86°F (15°-30°C)
- Avoid excessive heat

Inactive Ingredients

Flavor, Glycerin, PEG-1500, Silica, Sodium Benzoate, Sodium Carboxymethyl Cellulose, Sodium Lauryl Sulfate, Sodium Saccharin, Sorbitol, Tetra Sodium Pyrophosphate, Titanium Dioxide, Water